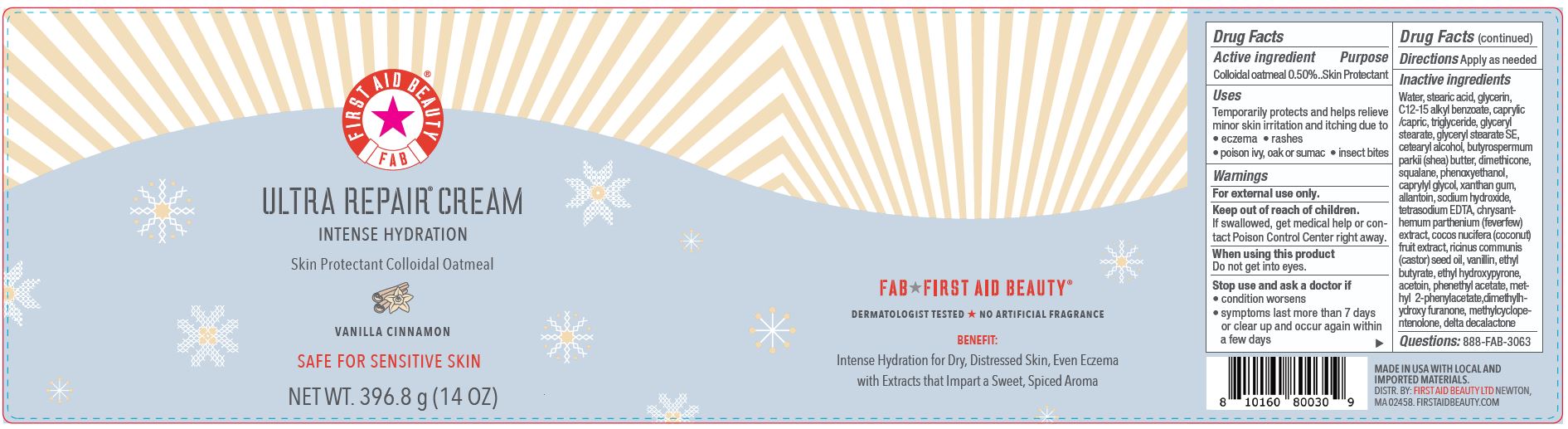 DRUG LABEL: First Aid Beauty FAB Ultra Repair Intense Hydration Skin Protectant Vanilla Cinnamon
NDC: 84126-048 | Form: CREAM
Manufacturer: The Procter & Gamble Manufacturing Company
Category: otc | Type: HUMAN OTC DRUG LABEL
Date: 20251218

ACTIVE INGREDIENTS: OATMEAL 0.5 g/100 g
INACTIVE INGREDIENTS: VANILLIN; ETHYL BUTYRATE; ETHYL HYDROXYPYRONE; SQUALANE; ACETOIN; RICINUS COMMUNIS (CASTOR) SEED OIL; PHENETHYL ACETATE; DIMETHYLHYDROXY FURANONE; GLYCERYL STEARATE SE; METHYLCYCLOPENTENOLONE; CETEARYL ALCOHOL; DIMETHICONE; TETRASODIUM EDTA; C12-15 ALKYL BENZOATE; CAPRYLYL GLYCOL; SODIUM HYDROXIDE; PHENOXYETHANOL; BUTYROSPERMUM PARKII (SHEA) BUTTER; WATER; GLYCERIN; ALLANTOIN; GLYCERYL STEARATE; CAPRYLIC/CAPRIC TRIGLYCERIDE; STEARIC ACID; XANTHAN GUM; CERAMIDE NP; TANACETUM PARTHENIUM WHOLE; COCOS NUCIFERA (COCONUT) FRUIT; DELTA-DECALACTONE; METHYL PHENYLACETATE

First Aid Beauty FAB Ultra Repair Cream Skin Protectant Vanilla Cinnamon

Drug Facts

Active ingredients

Colloidal Oatmeal 0.5%

Purpose

Skin Protectant

Uses

- Temporarily protects and helps relieve minor skin irritation and itching due to eczema, rashes, poison ivy, oak or sumac, insect bites

Warnings

For external use only.

Keep out of reach of children. If swallowed, get medical help or contact a Poison Control Center right away.

WHEN USING

Do not get into eyes.

Stop use and ask a doctor if condition worsens, symptoms last more than 7 days or clear up and occur again within a few days

Directions

Apply as needed

INACTIVE INGREDIENT

Water, stearic acid, glycerin, C12-15 alkyl benzoate, caprylic /capric, triglyceride, glyceryl stearate, glyceryl stearate SE, cetearyl alcohol, butyrospermum parkii (shea) butter, dimethicone, squalane, phenoxyethanol, caprylyl glycol, xanthan gum, allantoin, sodium hydroxide, tetrasodium EDTA, chrysanthemum parthenium (feverfew) extract, cocos nucifera (coconut) fruit extract, ricinus communis (castor) seed oil, vanillin, ethyl butyrate, ethyl hydroxypyrone, acetoin, phenethyl acetate, methyl 2-phenylacetate,dimethylhydroxy furanone, methylcyclopentenolone, delta decalactone

Questions:

888-FAB-3063

MADE IN USA

FIRST AID BEAUTY LTD

NEWTON, MA 02458

WWW.FIRSTAIDBEAUTY.COM

PRINCIPAL DISPLAY PANEL - 396.8 g (14 oz)

First Aid Beauty

FAB

Ultra Repair® Cream

Intense Hydration

Skin Protectant Colloidal Oatmeal

VANILLA CINNAMON

Net Wt. 396.8 g (14 oz)